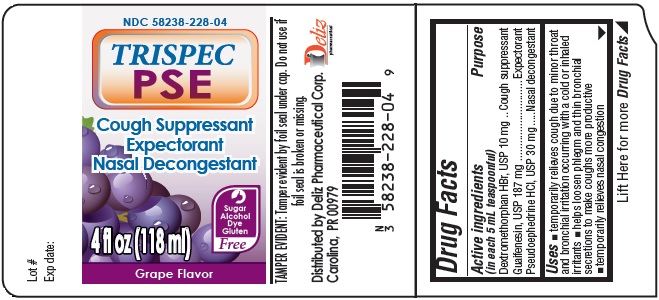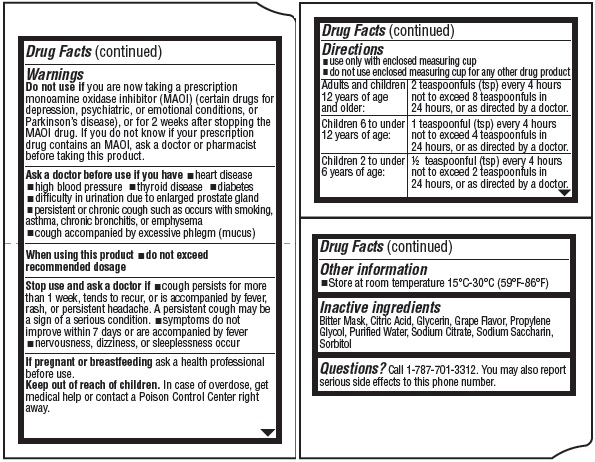 DRUG LABEL: TRISPEC PSE Cough Suppressant Expectorant Nasal Decongestant GRAPE Flavor
NDC: 58238-228 | Form: LIQUID
Manufacturer: Deliz Pharmaceutical Corp
Category: otc | Type: HUMAN OTC DRUG LABEL
Date: 20211102

ACTIVE INGREDIENTS: DEXTROMETHORPHAN HYDROBROMIDE 10 mg/5 mL; GUAIFENESIN 187 mg/5 mL; PSEUDOEPHEDRINE HYDROCHLORIDE 30 mg/5 mL
INACTIVE INGREDIENTS: CITRIC ACID MONOHYDRATE; PROPYLENE GLYCOL; WATER; SORBITOL; GLYCERIN; SODIUM CITRATE; SACCHARIN SODIUM

TRISPEC PSE Cough Suppressant Expectorant Nasal Decongestant GRAPE Flavor

Active ingredients (in each 5 mL teaspoonful)

Dextromethorphan HBr, USP 10 mg
Guaifenesin, USP 187 mg
Pseudoephedrine HCl, USP 30 mg

Purpose

Cough suppressant
Expectorant
Nasal decongestant

Uses

- temporarily relieves cough due to minor throat and bronchial irritation occuring with a cold or inhaled irritants
- helps loosen phlegm and thin bronchial secretions to make coughs more productive
- temporarily relieves nasal congestion

Warnings

Do not use if

you are now taking a prescription monoamine oxidase inhibitor (MAOI) (certain drugs for depression, psychiatric, or emotional conditions, or Parkinson’s disease), or for 2 weeks after stopping the MAOI drug. If you do not know if your prescription drug contains an MAOI, ask a doctor or pharmacist before taking this product.

Ask a doctor before use if

you have

- heart disease
- high blood pressure
- thyroid disease
- diabetes
- difﬁculty in urination due to enlarged prostate gland
- persistent or chronic cough such as occurs with smoking, asthma, chronic bronchitis, or emphysema
- cough accompanied by excessive phlegm (mucus)

_____________________________________________________________________________________________

When using this product

- do not exceed recommended dosage

Stop use and ask a doctor if

- cough persists for more than 1 week, tends to recur, or is accompanied by fever, rash, or persistent headache. A persistent cough may be a sign of a serious condition.
- symptoms do not improve within 7 days or are acompanied by fever
- nervousness, dizziness, or sleeplessness occur

If pregnant or breastfeeding

ask a health professional before use

Keep out of reach of children.

In case of overdose, get medical help or contact a Poison Control Center right away.

Directions

■ use only with enclosed measuring cup

■ do not use enclosed measuring cup for any other drug product

Adults and children 12 years of age and older: | 2 teaspoonfuls (tsp) every 4 hours not to exceed 8 teaspoonfuls in 24 hours, or as directed by a doctor.
Children 6 to under 12 years of age: | 1 teaspoonful (tsp) every 4 hours not to exceed 4 teaspoonfuls in 24 hours, or as directed by a doctor.
Children 2 to under 6 years of age: | ½ teaspoonful (tsp) every 4 hours not to exceed 2 teaspoonfuls in 24 hours, or as directed by a doctor.

Other Information

- Store at room temperature 15°C-30°C (59°F-86°F)

Inactive ingredients

Bitter Mask, Citric Acid, Glycerin, Grape Flavor, Propylene Glycol, Purified Water, Sodium Citrate, Sodium Saccharin, Sorbitol

Questions?

Call 1-787-701-3312. You may also report serious side effects to this phone number.